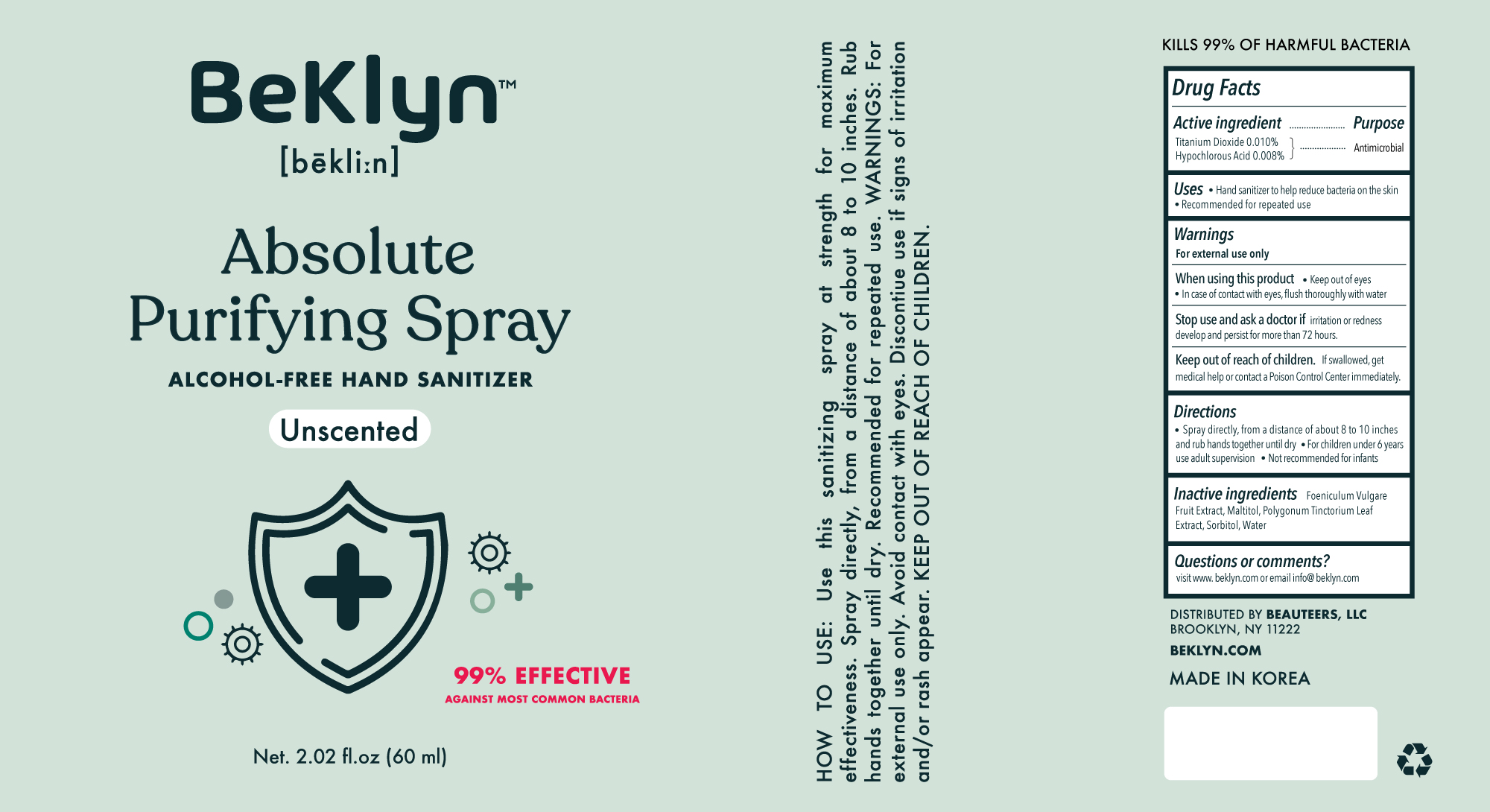 DRUG LABEL: Beklyn Absolute Purifying-Spray
NDC: 71544-0001 | Form: LIQUID
Manufacturer: MY Corp.,Ltd
Category: otc | Type: HUMAN OTC DRUG LABEL
Date: 20200715

ACTIVE INGREDIENTS: TITANIUM DIOXIDE 0.006 g/60 mL; HYPOCHLOROUS ACID 0.0048 g/60 mL
INACTIVE INGREDIENTS: FOENICULUM VULGARE FRUIT; MALTITOL; PERSICARIA TINCTORIA LEAF; SORBITOL; WATER

MY Corp - bekly spray 60ml

ACTIVE INGREDIENT

titanium dioxide, hypochlorous acid

INACTIVE INGREDIENT

Foeniculum Vulgare Fruit Extract, Maltitol, Polygonum Tinctorium Leaf Extract, Sorbitol, Water

PURPOSE

Hand sanitizer to help reduce bacteria that potentially can cause disease. Recommended for repeated use

keep out of reach of the children

INDICATIONS AND USAGE

- Spray directly, from a distance of about 8 to 10 inches and rub hands together until dry.
- For children under 6 years use adult supervision
- Not recommended for infants

WARNINGS

For external use only.

When using this product keep out of eyes, ears, and mouth. In case of contact with eyes, rinse thoroughly with water.

Stop use and ask a doctor if irritation or rash occurs develop and persist for more than 72 hours.

Keep out of reach of children. If swallowed, get medical help or contact a Poison Control Center right away.

DOSAGE AND ADMINISTRATION

for external use only